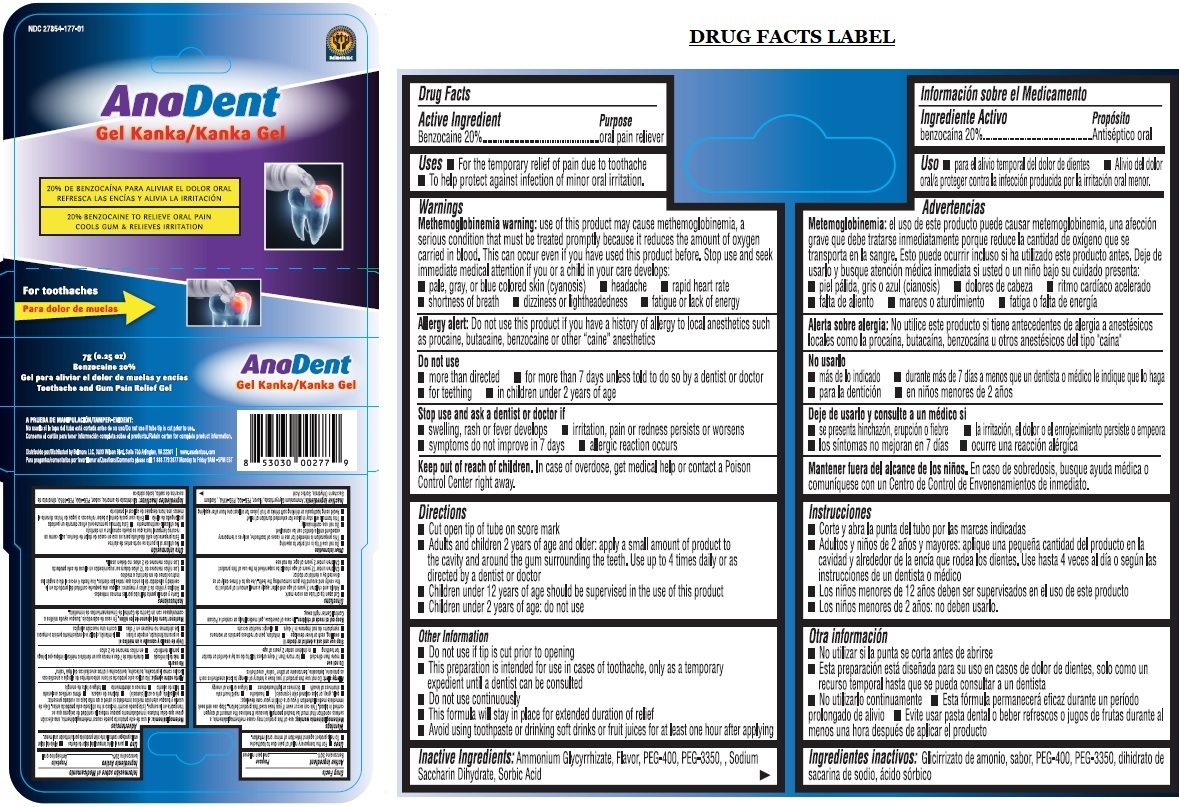 DRUG LABEL: Anadent Kanka Gel
NDC: 27854-177 | Form: GEL
Manufacturer: BELMORA LLC
Category: otc | Type: HUMAN OTC DRUG LABEL
Date: 20241004

ACTIVE INGREDIENTS: BENZOCAINE 200 mg/1 g
INACTIVE INGREDIENTS: AMMONIUM GLYCYRRHIZATE; POLYETHYLENE GLYCOL 400; POLYETHYLENE GLYCOL 3350; SACCHARIN SODIUM; SORBIC ACID

AnaDent Kanka Gel

Active Ingredient

Benzocaine 20%

Purpose

oral pain reliever

Uses

- For the temporary relief of pain due to toothache
- To help protect against infection of minor oral irritation.

Warnings

Methemoglobinemia warning: use of this product may cause methemoglobinemia, a serious condition that must be treated promptly because it reduces the amount of oxygen carried in blood. This can occur even if you have used this product before. Stop use and seek immediate medical attention if you or a child in your care develops:

- pale, gray, or blue colored skin (cyanosis) • headache • rapid heart rate
- shortness of breath • dizziness or lightheadedness • fatigue or lack of energy

Allergy alert: Do not use this product if you have a history of allergy to local anesthetics such as procaine, butacaine, benzocaine or other "caine" anesthetics

Do not use

- more than directed • for more than 7 days unless told to do so by a dentist or doctor
- for teething • in children under 2 years of age

Stop use and ask a dentist or doctor if

- swelling, rash or fever develops • irritation, pain or redness persists or worsens
- symptoms do not improve in 7 days • allergic reaction occurs

Keep out of reach of children. In case of overdose, get medical help or contact a Poison Control Center right away.

Directions

- Cut open tip of tube on score mark
- Adults and children 2 years of age and older: apply a small amount of product to the cavity and around the gum surrounding the teeth. Use up to 4 times daily or as directed by a dentist or doctor
- Children under 12 years of age should be supervised in the use of this product
- Children under 2 years of age: do not use

Other Information

- Do not use if tip is cut prior to opening
- This preparation is intended for use in cases of toothache, only as a temporary expedient until a dentist can be consulted
- Do not use continuously
- This formula will stay in place for extended duration of relief
- Avoid using toothpaste or drinking soft drinks or fruit juices for at least one hour after applying

Inactive Ingredients:

Ammonium Glycyrrhizate, Flavor, PEG-400, PEG-3350, Sodium Saccharin Dihydrate, Sorbic Acid

20% BENZOCAINE TO RELIEVE ORAL PAIN

COOLS GUM & RELIEVES IRRITATION

For toothaches

Toothache and Gum pain Relief Gel

TAMPER-EVIDENT:

Do not use if tube is cut prior to use.
Retain carton for complete product information.

Distributed by Belmora LLC, 3033 Wilson Blvd. Suite 700 Arlington, VA 22201 | www.anadentusa.com
Questions/Comments please call: 1 888 779 2877 Monday to Friday 9AM - 5PM EST